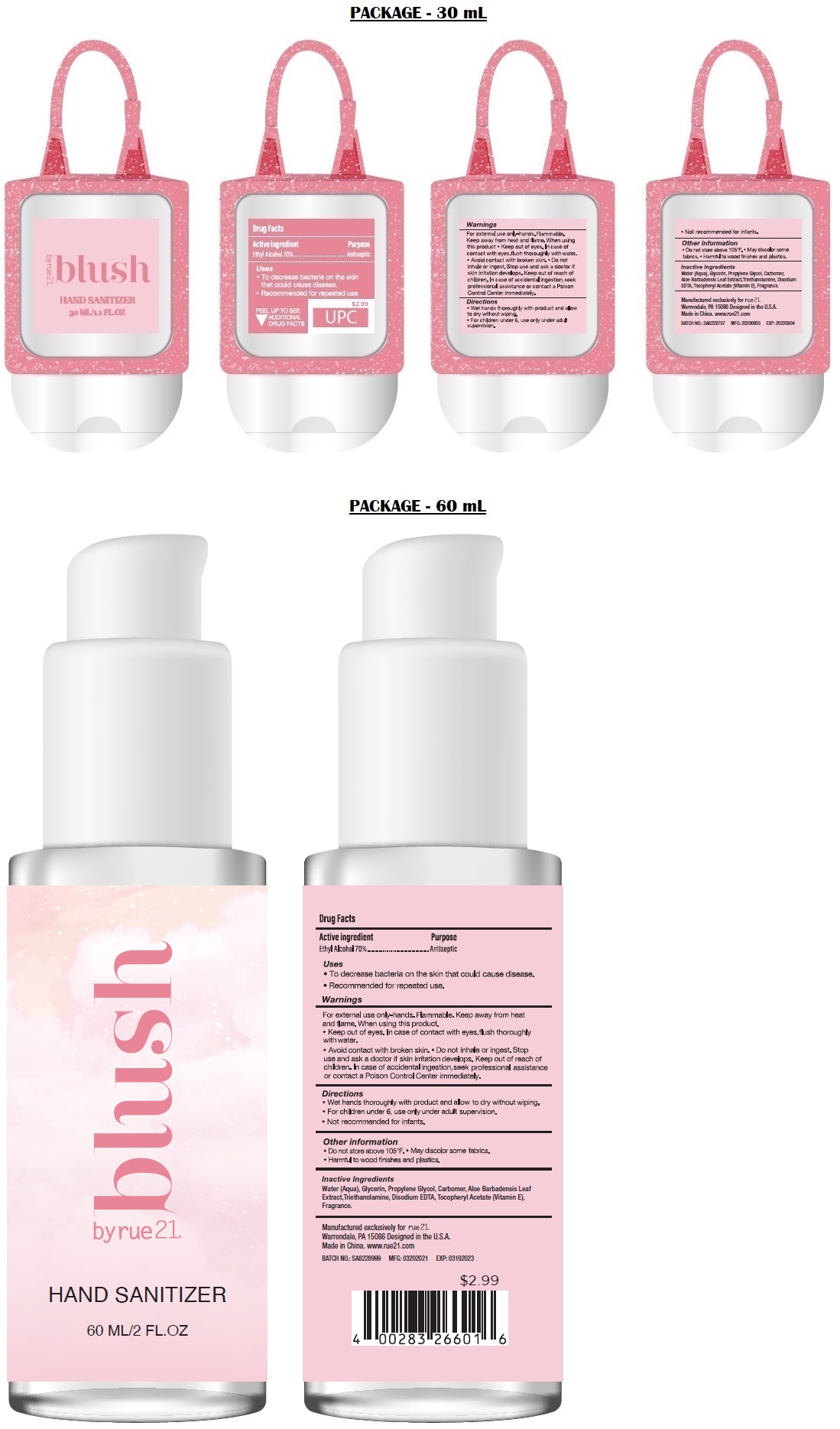 DRUG LABEL: rue21 BLUSH Hand Sanitizer
NDC: 69933-205 | Form: GEL
Manufacturer: Pearl World Inc.
Category: otc | Type: HUMAN OTC DRUG LABEL
Date: 20211103

ACTIVE INGREDIENTS: ALCOHOL 70 mL/100 mL
INACTIVE INGREDIENTS: WATER; GLYCERIN; PROPYLENE GLYCOL; CARBOMER HOMOPOLYMER, UNSPECIFIED TYPE; ALOE VERA LEAF; TROLAMINE; EDETATE DISODIUM ANHYDROUS; .ALPHA.-TOCOPHEROL ACETATE

BLUSH by rue21♥ HAND SANITIZER

Active ingredient

Ethyl Alcohol 70%

Purpose

Antiseptic

Uses

- To decrease bacteria on the skin that could cause disease.
- Recommended for repeated use.

Warnings

For external use only-hands. Flammable. Keep away from heat and flame. When using this product • Keep out of eyes. In case of contact with eyes, flush thoroughly with water. • Avoid contact with broken skin. • Do not inhale or ingest. Stop use and ask a doctor if skin irritation develops.

Keep out of reach of children. In case of accidental ingestion, seek professional assistance or contact a Poison Control Center immediately.

Directions

- Wet hands thoroughly with product and allow to dry without wiping.
- For children under 6, use only under adult supervision.
- Not recommended for infants.

Other information

• Do not store above 105°F. • May discolor some fabrics. • Harmful to wood finishes and plastics.

Inactive Ingredients

Water (Aqua), Glycerin, Propylene Glycol, Carbomer, Aloe Barbadensis Leaf Extract, Triethanolamine, Disodium EDTA, Tocopheryl Acetate (Vitamin E), Fragrance.

Manufactured exclusively for rue21®

Warrendale, PA 15086 Designed in the U.S.A.

Made in China. www.rue21.com